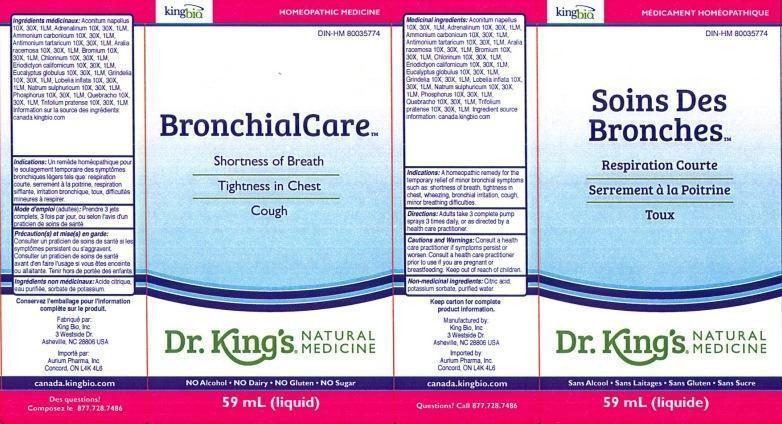 DRUG LABEL: BronchialCare Soins Des Bronches
NDC: 57955-1803 | Form: LIQUID
Manufacturer: King Bio Inc.
Category: homeopathic | Type: HUMAN OTC DRUG LABEL
Date: 20140821

ACTIVE INGREDIENTS: ACONITUM NAPELLUS 10 [hp_X]/59 mL; EPINEPHRINE 10 [hp_X]/59 mL; AMMONIUM CARBONATE 10 [hp_X]/59 mL; ANTIMONY POTASSIUM TARTRATE 10 [hp_X]/59 mL; ARALIA RACEMOSA ROOT 10 [hp_X]/59 mL; BROMINE 10 [hp_X]/59 mL; CHLORINE 10 [hp_X]/59 mL; ERIODICTYON CALIFORNICUM LEAF 10 [hp_X]/59 mL; EUCALYPTUS GLOBULUS LEAF 10 [hp_X]/59 mL; GRINDELIA HIRSUTULA FLOWERING TOP 10 [hp_X]/59 mL; LOBELIA INFLATA 10 [hp_X]/59 mL; SODIUM SULFATE 10 [hp_X]/59 mL; PHOSPHORUS 10 [hp_X]/59 mL; ASPIDOSPERMA QUEBRACHO-BLANCO BARK 10 [hp_X]/59 mL; TRIFOLIUM PRATENSE FLOWER 10 [hp_X]/59 mL
INACTIVE INGREDIENTS: CITRIC ACID MONOHYDRATE; POTASSIUM SORBATE; WATER

BronchialCare Soins Des Bronches

ACTIVE INGREDIENT

Medicinal ingredients/Ingrédients médicinaux: Aconitum napellus 10X, 30X, LM1, Adrenalinum 10X, 30X, LM1, Ammonium carbonicum 10X, 30X, LM1, Antimonium tartaricum 10X, 30X, LM1, Aralia racemosa 10X, 30X, LM1, Bromium 10X, 30X, LM1, Chlorinum 10X, 30X, LM1, Eriodictyon californicum 10X, 30X, LM1, Eucalyptus globulus 10X, 30X, LM1, Grindelia 10X, 30X, LM1, Lobelia inflata 10X, 30X, LM1, Natrum sulphuricum 10X, 30X, LM1, Phosphorus 10X, 30X, LM1, Quebracho 10X, 30X, LM1, Trifolium pratense 10X, 30X, LM1. Ingredient source information sur la source des ingrédients: canada.kingbio.com

INACTIVE INGREDIENT

Non-medicinal ingredients: Citric acid, potassium sorbate, purified water.

Ingrédients non médicinaux: acide citrique, eau purifiée, sorbate de potassium.

PURPOSE

Indications: A homeopathic remedy for the temporary relief of minor bronchial symptoms such as: shortness of breath, tighness in chest, wheezing, bronchial irritation, cough, minor breathing difficulties.

Indications: Un reméde homéopathique pour le soulagement temporaire des symptômes bronchiques légers tels que: respiration courte, serrement à la poitrine, respiration sifflante, irritation bronchique, toux, difficultés mineures à respirer.

DOSAGE AND ADMINISTRATION

Directions: Adults take 3 complete pump sprays, 3 times daily, or as directed by a health care practitioner.

Mode d'emploi (adultes): Prendre 3 jets complets, 3 fois par jour, ou selon l'avis d'un praticien de soins de santé.

INDICATIONS AND USAGE

Indications: A homeopathic remedy for the temporary relief of minor bronchial symptoms such as:

- shortness of breath
- tighness in chest
- wheezing
- bronchial irritation
- cough
- minor breathing difficulties

Indications: Un reméde homéopathique pour le soulagement temporaire des symptômes bronchiques légers tels que:

- respiration courte
- serrement à la poitrine
- respiration sifflante
- irritation bronchique
- toux
- difficultés mineures à respirer

WARNINGS

Cautions and Warnings: Consult a health care practitioner if symptoms persist or worsen. Consult a health care practitioner prior to use if you are pregnant or breastfeeding.

Précaution(s) et mise(s) en garde: Consulter un praticien de soins de santé si les symtômes persistent ou s'aggravent. Consulter un praticien de soins de santé avant d'en faire l'usage si vous êtes enceinte ou allaitante.

Keep out of reach of children.

Tenir hors de portée des enfants.